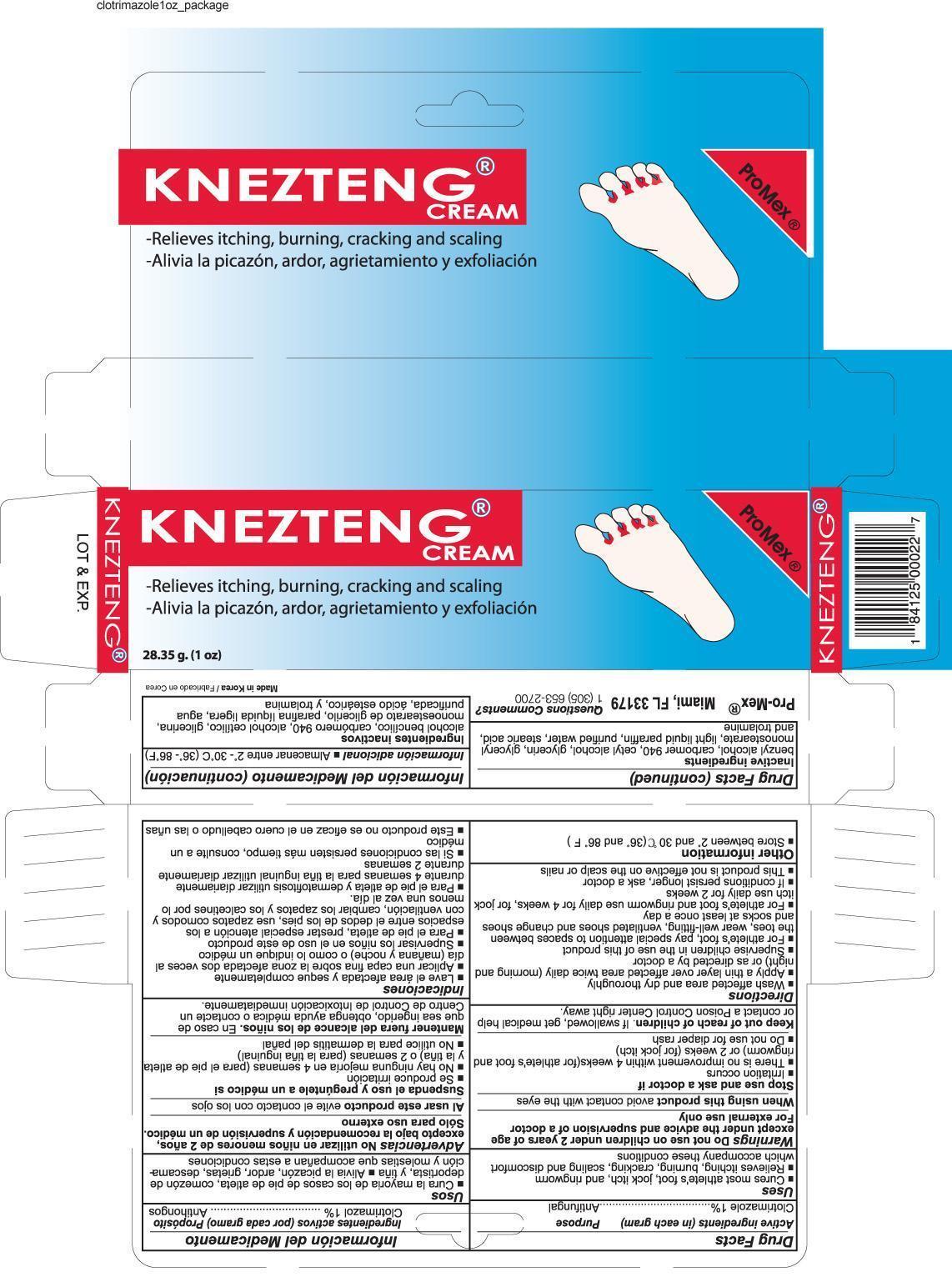 DRUG LABEL: Clotrimazole
NDC: 58988-0022 | Form: CREAM
Manufacturer: Promex, LLC
Category: otc | Type: HUMAN OTC DRUG LABEL
Date: 20131204

ACTIVE INGREDIENTS: Clotrimazole 1 g/100 g
INACTIVE INGREDIENTS: BENZYL ALCOHOL; CARBOMER HOMOPOLYMER TYPE C; CETYL ALCOHOL; GLYCERIN; GLYCERYL MONOSTEARATE; PARAFFIN; STEARIC ACID; TROLAMINE; WATER

Drug Facts

Active Ingredient

Clotrimazole 1%

Purpose

Antifungal

Uses

- Cures most athlete's foot, jock itch, and ringworm
- Relieves itching, burning, cracking, scaling and discomfort which accompany these conditions

Warnings

For external use only

Do not use

- on children under 2 years of age except under the advice and supervision of a doctor

When using this product

avoid contact with the eyes

Stop use and ask a doctor if

- Irritation occursThere is no improvement within 4 weeks(for athlete's foot and ringworm) or 2 weeks (for jock itch)Do not use for diaper rash

Keep out of reach of children

If swallowed, get medical help or contact a Poison Control Center right away.

Directions

- Wash affected area and dry thoroughly
- Apply a thin layer over affected area twice daily (morning and night) or as directed by a doctor
- Supervise children in the use of this product
- For athlete's foot, pay special attention to spaces between the toes, wear well-fitting, ventilated shoes and change shoes and socks at least once a day
- For athlete's foot and ringworm use daily for 4 weeks, for jock itch use daily for 2 weeks
- If conditions persist longer, ask a doctor
- This product is not effective on the scalp or nails

Other information

- store between 2°and 30°C (36°and 86°F)

Inactive ingredients

Benzyl alcohol, Carbomer940, Cetyl alcohol, Glycerin, Glyceryl monostearate, Light liquid paraffin, Purified water, Stearic acid and Trolamine

PACKAGE LABEL

Clotrimazole